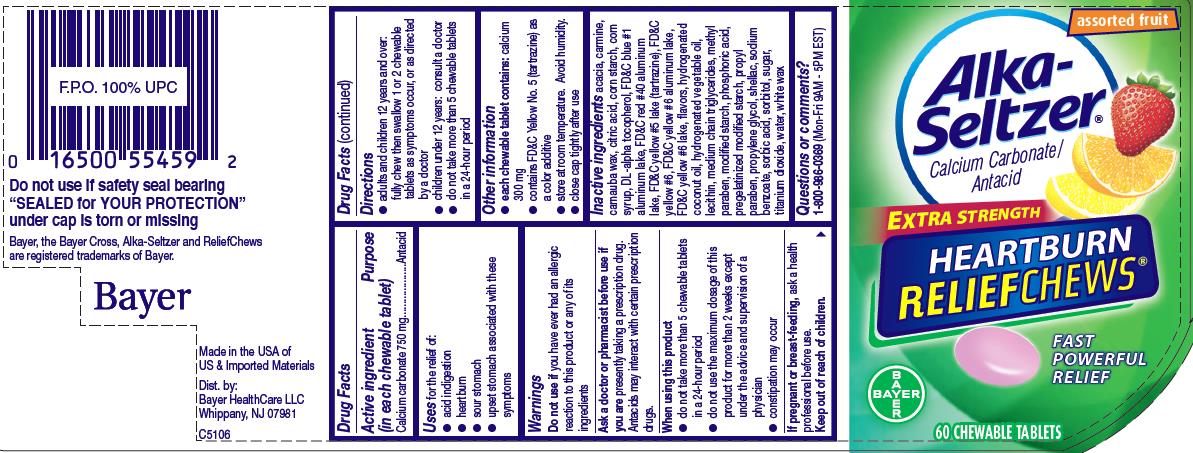 DRUG LABEL: Alka-Seltzer Extra Strength Heartburn ReliefChews
NDC: 0280-0042 | Form: TABLET, CHEWABLE
Manufacturer: Bayer HealthCare LLC.
Category: otc | Type: HUMAN OTC DRUG LABEL
Date: 20251204

ACTIVE INGREDIENTS: CALCIUM CARBONATE 750 mg/1 1
INACTIVE INGREDIENTS: ACACIA; SORBITOL; RAW SUGAR; WHITE WAX; TITANIUM DIOXIDE; FD&C BLUE NO. 1; FD&C RED NO. 40; FD&C YELLOW NO. 5; FD&C YELLOW NO. 6; CARNAUBA WAX; .ALPHA.-TOCOPHEROL, DL-; METHYLPARABEN; PROPYLPARABEN; HYDROGENATED COCONUT OIL; MODIFIED CORN STARCH (1-OCTENYL SUCCINIC ANHYDRIDE); CORN SYRUP; SHELLAC; SODIUM BENZOATE; SORBIC ACID; WATER; CARMINIC ACID; CITRIC ACID MONOHYDRATE; PROPYLENE GLYCOL; PHOSPHORIC ACID; MEDIUM-CHAIN TRIGLYCERIDES

Alka-Seltzer Extra Strength Heartburn ReliefChews

Active ingredient (in each chewable tablet)

Calcium carbonate 750 mg

Purpose

Antacid

Uses

for the relief of:

- acid indigestion
- heartburn
- sour stomach
- upset stomach associated with these symptoms

Warnings

Do not use if

you have ever had an allergic reaction to this product or any of its ingredients

Ask a doctor or pharmacist before use if you are

presently taking a prescription drug. Antacids may interact with certain prescription drugs.

When using this product

- do not take more than 5 chewable tablets in a 24-hour period
- do not use the maximum dosage of this product for more than 2 weeks except under the advice and supervision of a physician
- constipation may occur

If pregnant or breast-feeding, ask a health professional before use.

Keep out of reach of children

Directions

- adults and children 12 years and over: fully chew then swallow 1 or 2 chewable tablets as symptoms occur, or as directed by as doctor
- children under 12 years: consult a doctor
- do not take more than 5 chewable tablets in a 24-hour period

Other information

- each chewable tablet contains: calcium 300 mg
- contains FD&C Yellow No. 5 (tartrazine) as a color additive
- store at room temperature. Avoid humidity.
- close cap tightly after use

Inactive ingredients

acacia, carmine, carnauba wax, citric acid, corn starch, corn syrup, DL-alpha tocopherol, FD&C blue #1 aluminum lake, FD&C red #40 aluminum lake, FD&C yellow #5 lake (tartrazine), FD&C yellow #6, FD&C yellow #6 aluminum lake, FD&C yellow #6 lake, flavors, hydrogenated coconut oil, hydrogenated vegetable oil, lecithin, medium chain triglycerides, methyl paraben, modified starch, phosphoric acid, pregelatinized modified starch, propyl paraben, propylene glycol, shellac, sodium benzoate, sorbic acid, sorbitol, sugar, titanium dioxide, water, white wax

Questions or comments?

1-800-986-0369 (Mon-Fri 9AM - 5PM EST)

Principle display panel

assorted fruit

Alka-Seltzer

Calcium Carbonate / Antacid

Extra Strength

Heartburn ReliefChews

Fast

Powerful

relief

Bayer

60 CHEWABLE TABLETS